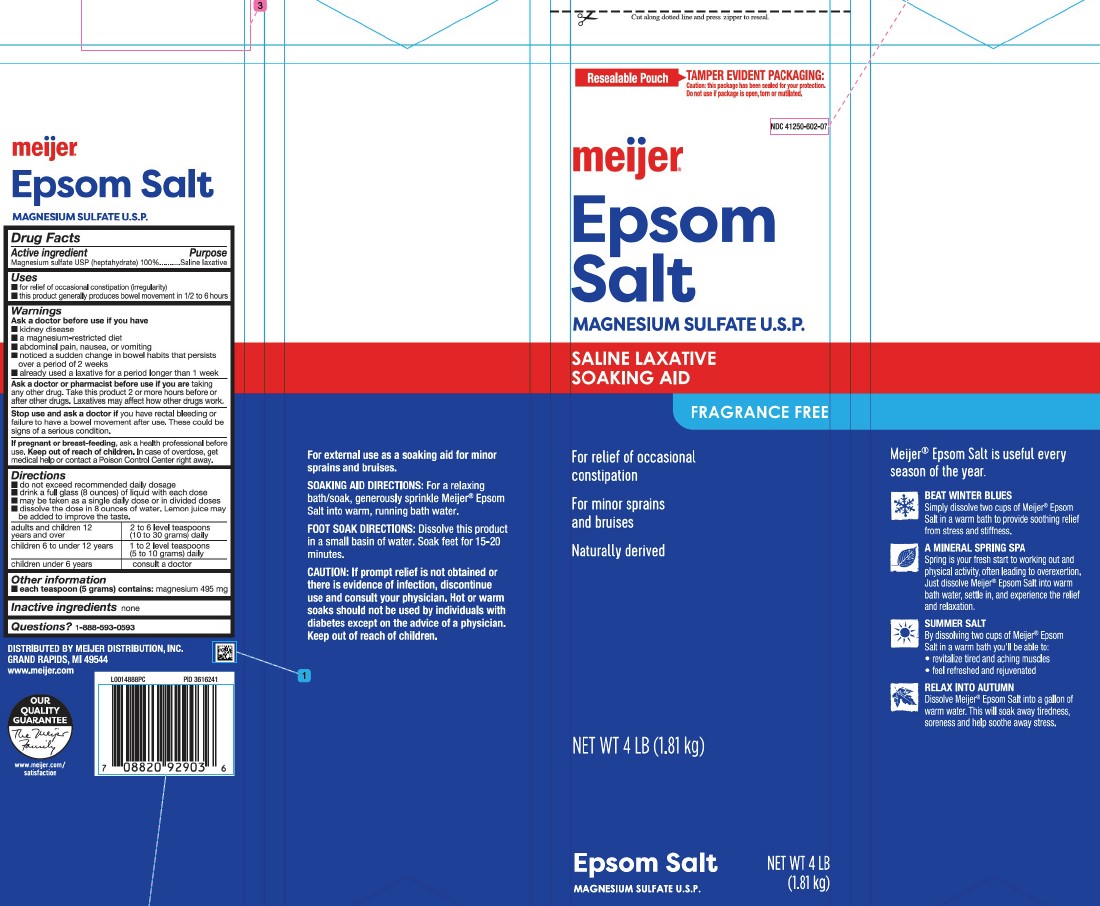 DRUG LABEL: Epsom Salt
NDC: 41250-602 | Form: GRANULE, FOR SOLUTION
Manufacturer: Meijer, Inc.
Category: otc | Type: HUMAN OTC DRUG LABEL
Date: 20260219

ACTIVE INGREDIENTS: MAGNESIUM SULFATE HEPTAHYDRATE 1 g/1 g

Meijer 602.002/602AA
Epsom Salt

Claims

meijer®

Epsom Salt

MAGNESIUM SULFATE U.S.P.

Active ingredient

Magnesium sulfate USP (heptahydrate) 100%

Purpose

Saline Laxative

Uses

- for relief of occasional constipation (irregularity)
- this product generally produces bowel movement in 1/2 to 6 hours

Warnings

for this product

Ask a doctor before use if you have

- kidney disease
- a magnesium-restricted diet
- abdominal pain, nausea, or vomiting
- noticed a sudden change in bowel habits that persists over a period of 2 weeks
- already used a laxative for a period longer than 1 week

Ask a doctor or pharmacist before use if you are

taking any other drug. Take this product 2 or more hours before or after other drugs. Laxatives may affect how other drugs work.

Stop use and ask a doctor if

you have rectal bleeding or failure to have a bowel movement after use. These could be signs of a serious condition.

If pregnant or breast-feeding,

ask a health professional before use.

Keep out of reach of children.

In case of overdose, get medical help or contact a Poison Control Center right away.

Directions

- do not exceed recommended daily dosage
- drink a full glass (8 ounces) of liquid with each dose
- may be taken as a single daily dose or in divided doses
- dissolve the dose in 8 ounces of water. Lemon juice may be added to improve the taste

adults and children 12 years and over - 2 to 6 level teaspoons (10 to 30 grams) daily

children 6 to under 12 years - 1 to 2 level teaspoons (5 to 10 grams) daily

children under 6 years - consult a doctor

inactive ingredient

none

Other information

- each teaspoon (5 grams) contains: magnesium 495 mg

Questions

1-888-593-0593

Side panels

For external use as a soaking aid for minor sprains and bruises.

Soaking Aid Directions: For a relaxing bath/soak, generously sprinkle Meijer® Epsom Salt into warm, running bath water.

Foot Soak Directions: Dissolve this product in a small basin of water. Soak for 15-20 minutes.

CAUTION: If prompt relief is not obtained or there is evidence of infection, discontinue use and consult your physician. Hot or warms soaks should not be used by individuals with diabetes except on the advice of a physican.

Keep out of children.

Meijer®Epsom Salt is useful every season of the year.

BEAT WINTER BLUES
Simply dissolve two cups of Meijer®Epsom Salt in a warm bath to provide soothing relief from stress stiffness.

A MINERAL SPRING SPA
Spring is your fresh start to working out and physical activity, often leading to overexertion. Just dissolve two cups of Meijer®Epsom Salt into warm bath water, settle in, and experience the relief and relaxation.

FIRST AID SUMMER SALT
By dissolving two cups of Meijer®Epsom Salt in a warm bath you'll be able to:

- revitalize tired and aching muscles
- feel refreshed and rejuvenated

RELAX INTO AUTUMN
Dissolve two cups of Meijer®Epsom Salt into a gallon of war water. This will soak away tiredness, soreness and help soothe away stress.

Adverse reaction

DIST. BY MEIJER DISTRIBUTION, INC.

GRAND RAPIDS, MI 49544

www.meijer.com

OUR QUALITY GUARANTEE

The Meijer Family

www.meijer.com/satisfaction

principal panel display

Cut along dotted line and press zipper to reseal.

Resealable Pouch

TAMPER EVIDENT PACKAGING:

Caution: this package has been sealed for your protection. Do not use if package is open, torn or mutilated.

NDC 41250-602-07

meijer®

Epsom Salt

Magnesium Sulfate U.S.P.

Saline Laxative

Soaking Aid

FRAGRANCE FREE

For Relief of Occasional Constipation

For minor Sprains and Bruises

Naturally derived

NET WT 4 LB (1.81 kg)

Epsom Salt

Magnesium Sulfate U.S.P.

NET WT 4 LB (1.81 kg)